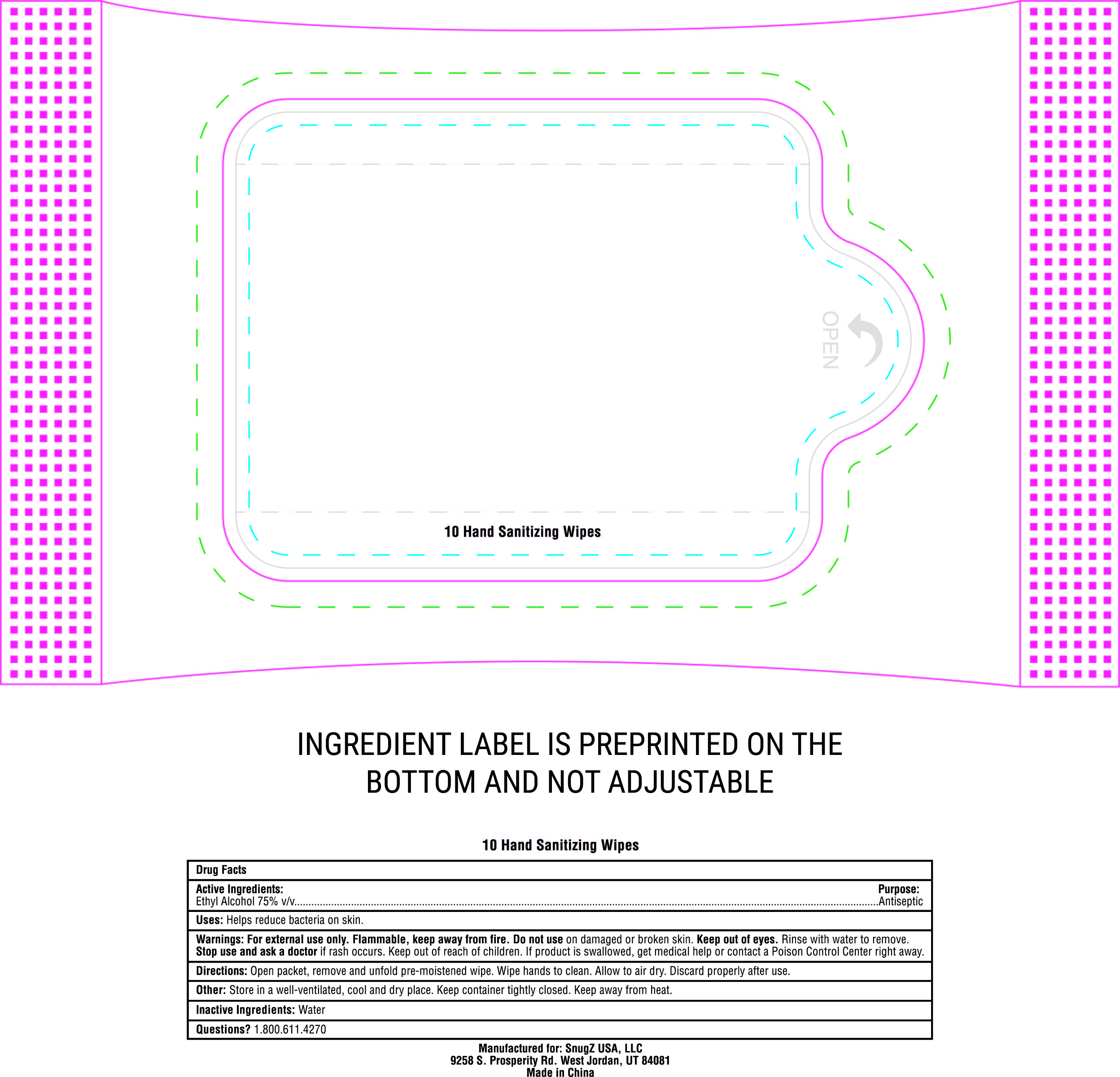 DRUG LABEL: SnugZ Hand Sanitizing Wipes
NDC: 76309-700 | Form: CLOTH
Manufacturer: SnugZ/USA, LLC
Category: otc | Type: HUMAN OTC DRUG LABEL
Date: 20251229

ACTIVE INGREDIENTS: ALCOHOL 75 mL/100 mL
INACTIVE INGREDIENTS: WATER

Hand Sanitizing Wipes

SnugZ Hand Sanitizing Wipes

Ethyl Alcohol 75% v/v.........................................Antiseptic

SnugZ Hand Sanitizing Wipes

Help reduce bacteria on skin.

SnugZ Hand Sanitizing Wipes

For external use only. Flammable, keep away from fire. Do not use on damaged or broken skin. Keep out of eyes. Rinse with water to remove. Stop use and ask a doctor if rash occurs. If product is swallowed, get medical help or contact a Poison Control Center right away.

Keep Out of Reach of Children

Warnings: Keep out of reach of children.

Directions

Directions: Open packet, remove and unfold pre-moistened wipe. Wipe hands to clean. Allow to air dry. Discard properly after use.

Uses

Uses: Helps reduce bacteria on skin.

Inactive Ingredients:

Inactive Ingredients: Water